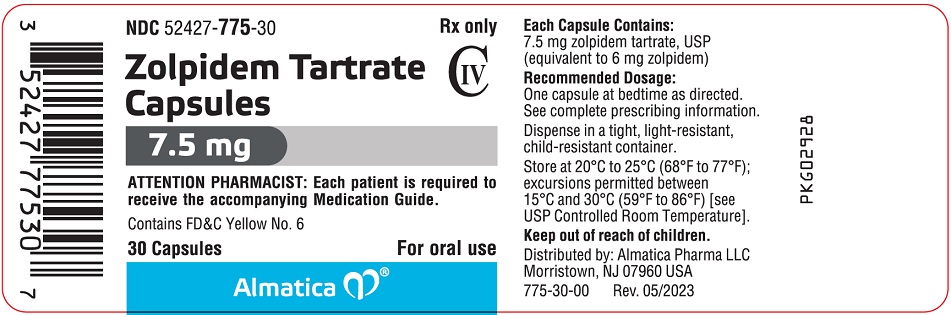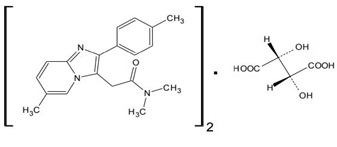 DRUG LABEL: zolpidem tartrate
NDC: 52427-775 | Form: CAPSULE
Manufacturer: Almatica Pharma LLC
Category: prescription | Type: HUMAN PRESCRIPTION DRUG LABEL
Date: 20251009
DEA Schedule: CIV

ACTIVE INGREDIENTS: ZOLPIDEM TARTRATE 7.5 mg/1 1
INACTIVE INGREDIENTS: GELATIN, UNSPECIFIED; LACTOSE MONOHYDRATE; MAGNESIUM STEARATE; MICROCRYSTALLINE CELLULOSE; SODIUM STARCH GLYCOLATE TYPE A; TITANIUM DIOXIDE; FD&C BLUE NO. 1; FD&C RED NO. 40; FD&C YELLOW NO. 6

HIGHLIGHTS OF PRESCRIBING INFORMATION

These highlights do not include all the information needed to use ZOLPIDEM TARTRATE CAPSULES safely and effectively. See full prescribing information for ZOLPIDEM TARTRATE CAPSULES.
ZOLPIDEM TARTRATE capsules, for oral use, CIV
Initial U.S. Approval: 1992

WARNING: COMPLEX SLEEP BEHAVIORS

See full prescribing information for complete boxed warning.

Complex sleep behaviors including sleep-walking, sleep-driving, and engaging in other activities while not fully awake may occur following use of Zolpidem Tartrate Capsules. Some of these events may result in serious injuries, including death. Discontinue Zolpidem Tartrate Capsules immediately if a patient experiences a complex sleep behavior. (4, 5.1)

1 INDICATIONS AND USAGE

Zolpidem Tartrate Capsules, a gamma-aminobutyric acid (GABA) A receptor positive modulator, is indicated for the short-term treatment of transient insomnia characterized by difficulties with sleep initiation in adults younger than 65 years of age (1)

2 DOSAGE AND ADMINISTRATION

- Zolpidem Tartrate Capsules are only available in 7.5 mg strength. Use another zolpidem tartrate immediate-release product for 5 mg or 10 mg dosage (2.1)
- Avoid use of Zolpidem Tartrate Capsules in geriatric patients (2.1)
- Recommended dosage of zolpidem tartrate (use the lowest effective zolpidem tartrate dosage):
  - Females: The recommended starting dosage of zolpidem tartrate immediate-release in females is 5 mg once nightly. Use another zolpidem tartrate immediate-release product for dosage initiation in females (2.1, 2.2, 8.6)
  - Males: The recommended starting dosage of zolpidem tartrate immediate-release in males is either zolpidem tartrate immediate-release 5 mg, Zolpidem Tartrate Capsules 7.5 mg, or zolpidem tartrate immediate-release 10 mg, once nightly. Use another zolpidem tartrate immediate-release product for 5 mg and 10 mg dosing (2.2)
  - In both males and females: If a 5 mg nightly dose of another zolpidem tartrate immediate-release product is not effective, the zolpidem tartrate dosage may be increased to Zolpidem Tartrate Capsules 7.5 mg once nightly or 10 mg once nightly of another zolpidem tartrate immediate-release product. The maximum recommended dosage of zolpidem tartrate immediate-release is 10 mg once nightly (2.2)
- Zolpidem Tartrate Capsules are for short-term use only (2.3)
- Administer Zolpidem Tartrate Capsules orally once per night immediately before bedtime with at least 7 to 8 hours remaining before the planned time of awakening (2.4)
- Zolpidem Tartrate Capsules should not be taken with or immediately after a meal. Swallow whole. Do not open, crush, or chew (2.4)
- Lower doses of CNS depressants may be necessary when taken concomitantly with Zolpidem Tartrate Capsules (2.5)

3 DOSAGE FORMS AND STRENGTHS

Capsules: 7.5 mg (3)

4 CONTRAINDICATIONS

- Patients who have experienced complex sleep behaviors after taking zolpidem (4)
- Known hypersensitivity to zolpidem (4)

5 WARNINGS AND PRECAUTIONS

- CNS-Depressant Effects: Impaired alertness and motor coordination including risk of morning impairment. Risk increases with dose and use with other CNS depressants and alcohol. Caution patients against driving and other activities requiring mental alertness the morning after use. Instruct patients on correct use (5.2)
- Need to Evaluate for Comorbid Diagnoses: Reevaluate if insomnia persists after 7 to 10 days of use (5.3)
- Severe Anaphylactic/Anaphylactoid Reactions: Angioedema and anaphylaxis have been reported. Do not rechallenge if such reactions occur (5.4)
- Abnormal Thinking and Behavioral Changes: Changes including decreased inhibition, bizarre behavior, agitation, and depersonalization have been reported. Immediately evaluate any new onset behavioral changes (5.5)
- Depression: Worsening of depression or suicidal thinking may occur. Prescribe the least amount of capsules feasible to avoid intentional overdose (5.6)
- Respiratory Depression: Consider this risk before prescribing in patients with compromised respiratory function (5.7)
- Precipitation of Hepatic Encephalopathy: Avoid zolpidem tartrate in patients with severe hepatic impairment (2.1, 5.8, 8.7)
- Withdrawal Effects: Symptoms may occur with rapid dose reduction or discontinuation (5.9, 9.3)

6 ADVERSE REACTIONS

Most commonly observed adverse reactions: headache, drowsiness, dizziness, and diarrhea (6.1)

To report SUSPECTED ADVERSE REACTIONS, contact Almatica Pharma LLC at 1-877-447-7979 or FDA at 1-800-FDA-1088 or www.fda.gov/medwatch.

7 DRUG INTERACTIONS

- CNS depressants, including alcohol: Possible adverse additive CNS-depressant effects. Dose adjustment may be necessary (2.5, 5.2, 7)
- Opioids: Concomitant use may increase risk of respiratory depression (5.7, 7)
- Imipramine: Decreased alertness observed (7)
- Chlorpromazine: Impaired alertness and psychomotor performance observed (7)
- CYP3A4 inducers: Combination use may decrease effect (7)
- CYP3A4 inhibitors: Combination use may increase effect (7)

8 USE IN SPECIFIC POPULATIONS

- Pregnancy: May cause respiratory depression and sedation in neonates with exposure late in the third trimester (8.1)
- Lactation: A lactating woman may pump and discard breast milk during treatment and for 23 hours after Zolpidem Tartrate Capsule administration (8.2)
- Hepatic Impairment: Avoid use (2.1, 8.7)
- Pediatric use: Safety and effectiveness not established. Hallucinations (incidence rate 7%) and other psychiatric and/or nervous system adverse reactions were observed frequently in a study of pediatric patients with Attention-Deficit/Hyperactivity Disorder (5.5, 8.4)

FULL PRESCRIBING INFORMATION

WARNING: COMPLEX SLEEP BEHAVIORS

Complex sleep behaviors including sleep-walking, sleep-driving, and engaging in other activities while not fully awake may occur following use of Zolpidem Tartrate Capsules. Some of these events may result in serious injuries, including death. Discontinue Zolpidem Tartrate Capsules immediately if a patient experiences a complex sleep behavior [see Contraindications (4) and Warnings and Precautions (5.1)].

1 INDICATIONS AND USAGE

Zolpidem Tartrate Capsules are indicated for the short-term treatment of transient insomnia characterized by difficulties with sleep initiation in adults younger than 65 years of age [see Dosage and Administration (2.1) and Clinical Studies (14)].

2 DOSAGE AND ADMINISTRATION

2.1 Important Dosage Information

Zolpidem Tartrate Capsules are only available in a 7.5 mg strength. Use another zolpidem tartrate immediate-release product for the 5 mg or 10 mg dose of zolpidem tartrate immediate-release. Refer to the Prescribing Information of other zolpidem tartrate immediate-release products for the recommended dosage for those products.

- Zolpidem Tartrate Capsules are not indicated in geriatric patients. Avoid use of Zolpidem Tartrate Capsules in geriatric patients because the recommended dosage in these patients cannot be achieved with the Zolpidem Tartrate Capsules 7.5 mg strength [see Use in Specific Populations (8.5)]. Use another zolpidem tartrate product for geriatric patients.
- The recommended starting dosage for females is different than males because zolpidem clearance is lower in females [see Use in Specific Populations (8.7) and Clinical Pharmacology (12.3)]. Do not use Zolpidem Tartrate Capsules to initiate zolpidem tartrate treatment in females because the recommended starting dosage in females cannot be achieved with the Zolpidem Tartrate Capsules 7.5 mg strength. Use another zolpidem tartrate immediate-release product to initiate treatment in females [see Dosage and Administration (2.2)].
- Avoid Zolpidem Tartrate Capsules in patients with mild or moderate hepatic impairment because the recommended dosage in such patients cannot be achieved with the Zolpidem Tartrate Capsules 7.5 mg strength [see Warnings and Precautions (5.8), Use in Specific Populations (8.7) and Clinical Pharmacology (12.3)].
- Avoid any zolpidem tartrate use in patients with severe hepatic impairment because its use may contribute to encephalopathy [see Warnings and Precautions (5.8), Use in Specific Populations (8.7), Clinical Pharmacology (12.3)].

2.2 Recommended Dosage

Use the lowest effective zolpidem tartrate dosage. For instructions on administration of Zolpidem Tartrate Capsules, see Dosage and Administration (2.4).

- The recommended starting dosage of zolpidem tartrate immediate-release in females is 5 mg once nightly. Use another zolpidem tartrate immediate-release product for dosage initiation in females [see Use in Specific Populations (8.6) and Clinical Pharmacology (12.3)].
- The recommended starting dosage of zolpidem tartrate immediate-release in males is either zolpidem tartrate immediate-release 5 mg, Zolpidem Tartrate Capsules 7.5 mg, or zolpidem tartrate immediate-release 10 mg, once nightly.

In both males and females, if a 5 mg once nightly dose of another zolpidem tartrate immediate-release product is not effective, the zolpidem tartrate dosage may be increased to Zolpidem Tartrate Capsules 7.5 mg once nightly or 10 mg once nightly of another zolpidem tartrate immediate-release product. The maximum recommended dosage of zolpidem tartrate immediate-release is 10 mg once nightly.

Zolpidem Tartrate Capsules should be taken as a single dose and should not be readministered during the same night.

2.3 Recommended Duration of Treatment

Zolpidem Tartrate Capsules are for short-term use only. Re-evaluate the patient’s status during treatment because the risk of abuse and dependence increases with duration of treatment [see Drug Abuse and Dependence (9.3)].

2.4 Administration Instructions

Administer Zolpidem Tartrate Capsules orally once per night immediately before bedtime with at least 7 to 8 hours remaining before the planned time of awakening [see Warnings and Precautions (5.2)].

Zolpidem Tartrate Capsules should not be administered with food or immediately after a meal [see Clinical Pharmacology (12.3)]. Swallow Zolpidem Tartrate Capsules whole; do not open, crush, or chew.

2.5 Dosage Modifications with CNS Depressants

Dosage modifications may be necessary when Zolpidem Tartrate Capsules are combined with other CNS-depressant drugs because of the potentially additive effects [see Warnings and Precautions (5.2, 5.7)]. Use another zolpidem tartrate immediate-release product for the 5 mg dosage of zolpidem tartrate immediate-release. Refer to the Prescribing Information of other zolpidem tartrate immediate-release products for the recommended dosage for those products.

3 DOSAGE FORMS AND STRENGTHS

Capsules: 7.5 mg, hard gelatin capsules with "ALM" printed axially on the opaque light green cap and "775" printed axially on the opaque white body. All printing is in grey ink.

4 CONTRAINDICATIONS

Zolpidem Tartrate Capsules are contraindicated in patients:

- who have experienced complex sleep behaviors after taking zolpidem [see Warnings and Precautions (5.1)].
- with known hypersensitivity to zolpidem. Observed reactions include anaphylaxis and angioedema [see Warnings and Precautions (5.4)].

5 WARNINGS AND PRECAUTIONS

5.1 Complex Sleep Behaviors

Complex sleep behaviors, including sleep-walking, sleep-driving, and engaging in other activities while not fully awake, may occur following the first or any subsequent use of Zolpidem Tartrate Capsules. Patients can be seriously injured or injure others during complex sleep behaviors. Such injuries may result in a fatal outcome. Other complex sleep behaviors (e.g., preparing and eating food, making phone calls, or having sex) have also been reported. Patients usually do not remember these events. Postmarketing reports have shown that complex sleep behaviors may occur with zolpidem alone at recommended dosage, with or without the concomitant use of alcohol or other central nervous system (CNS) depressants [see Drug Interactions (7)]. Discontinue Zolpidem Tartrate Capsules immediately if a patient experiences a complex sleep behavior [see Contraindications (4)].

5.2 CNS-Depressant Effects and Next-Day Impairment

Zolpidem tartrate, like other sedative-hypnotic drugs, has CNS-depressant effects. Coadministration with other CNS depressants (e.g., benzodiazepines, opioids, tricyclic antidepressants, alcohol) increases the risk of CNS depression [see Drug Interactions (7)]. Dosage adjustments of zolpidem tartrate and of other concomitant CNS depressants may be necessary when Zolpidem Tartrate Capsules are administered with such agents because of the potentially additive effects. Use another zolpidem tartrate immediate-release product for the 5 mg dose of zolpidem tartrate immediate-release. Refer to the Prescribing Information of other zolpidem tartrate immediate-release products for the recommended dosage for those products. The use of Zolpidem Tartrate Capsules with other sedative-hypnotics (including other zolpidem products) at bedtime or the middle of the night is not recommended [see Dosage and Administration (2.5)].

The risk of next-day psychomotor impairment, including impaired driving, is increased if Zolpidem Tartrate Capsules are taken with less than a full night of sleep remaining (7 to 8 hours); if a higher than the recommended dosage is taken; if coadministered with other CNS depressants or alcohol; or if coadministered with other drugs that increase the blood levels of zolpidem. Patients should be warned against driving and other activities requiring complete mental alertness if Zolpidem Tartrate Capsules are taken in these circumstances [see Dosage and Administration (2.5), Clinical Studies (14.2)]. Vehicle drivers and machine operators should be warned that, as with other hypnotics, there may be a possible risk of adverse reactions including drowsiness, prolonged reaction time, dizziness, sleepiness, blurred/double vision, reduced alertness, and impaired driving the morning after therapy. In order to minimize this risk a full night of sleep (7 to 8 hours) is recommended.

Because Zolpidem Tartrate Capsules can cause drowsiness and a decreased level of consciousness, patients, particularly the elderly, are at higher risk of falls.

5.3 Need to Evaluate for Comorbid Diagnoses

Because sleep disturbances may be the presenting manifestation of a physical and/or psychiatric disorder, symptomatic treatment of insomnia should be initiated only after a careful evaluation of the patient. The failure of insomnia to remit after 7 to 10 days of Zolpidem Tartrate Capsules treatment may indicate the presence of a primary psychiatric and/or medical illness that should be evaluated. Worsening of insomnia or the emergence of new thinking or behavior abnormalities may be the consequence of an unrecognized psychiatric or physical disorder. Such findings have emerged during the course of treatment with sedative/hypnotic drugs, including zolpidem tartrate.

5.4 Severe Anaphylactic and Anaphylactoid Reactions

Cases of angioedema involving the tongue, glottis or larynx have been reported in patients after taking the first or subsequent doses of sedative-hypnotics, including zolpidem tartrate. Some patients have had additional symptoms such as dyspnea, throat closing or nausea and vomiting that suggest anaphylaxis. Some patients have required medical therapy in the emergency department. If angioedema involves the throat, glottis or larynx, airway obstruction may occur and be fatal. Patients who develop angioedema after treatment with Zolpidem Tartrate Capsules should not be rechallenged with zolpidem tartrate.

5.5 Abnormal Thinking and Behavioral Changes

Abnormal thinking and behavior changes have been reported in patients treated with sedative/hypnotics, including zolpidem tartrate immediate-release. Some of these changes included decreased inhibition (e.g., aggressiveness and extroversion that seemed out of character), bizarre behavior, agitation and depersonalization. Visual and auditory hallucinations have been reported.

In controlled trials of zolpidem tartrate immediate-release 10 mg taken at bedtime <1% of adults with insomnia reported hallucinations. In a clinical trial, 7% of pediatric patients treated with zolpidem tartrate immediate-release 0.25 mg/kg taken at bedtime reported hallucinations versus 0% treated with placebo (Zolpidem Tartrate Capsules are not approved for use in pediatric patients) [see Use in Specific Populations (8.4)]. There have been postmarketing reports of delirium with zolpidem tartrate use [see Adverse Reactions (6.2)].

It can rarely be determined with certainty whether a particular instance of the abnormal behaviors listed above is drug induced, spontaneous in origin, or a result of an underlying psychiatric or physical disorder. Nonetheless, the emergence of any new behavioral sign or symptom of concern requires careful and immediate evaluation.

5.6 Use in Patients with Depression

In primarily depressed patients treated with sedative-hypnotics, worsening of depression, and suicidal thoughts and actions (including completed suicides), have been reported. Suicidal tendencies may be present in such patients and protective measures may be required. Intentional overdosage is more common in this group of patients; therefore, the lowest number of Zolpidem Tartrate Capsules that is feasible should be prescribed for the patient at any one time.

5.7 Respiratory Depression

Although studies with 10 mg zolpidem tartrate immediate-release did not reveal respiratory depressant effects at hypnotic doses in healthy subjects or in patients with mild to moderate chronic obstructive pulmonary disease (COPD), a reduction in the Total Arousal Index, together with a reduction in lowest oxygen saturation and increase in the times of oxygen desaturation below 80% and 90%, was observed in patients with mild to moderate sleep apnea when treated with zolpidem tartrate immediate-release compared to placebo. Since sedative-hypnotics have the capacity to depress respiratory drive, precautions should be taken if Zolpidem Tartrate Capsules are prescribed to patients with compromised respiratory function or concomitant use with opioids or other CNS depressants. Postmarketing reports of respiratory insufficiency in patients receiving 10 mg of zolpidem tartrate immediate-release, most of whom had pre-existing respiratory impairment, have been reported. The risk of respiratory depression should be considered prior to prescribing Zolpidem Tartrate Capsules in patients with respiratory impairment including sleep apnea and myasthenia gravis or with concomitant opioid use [see Dosage and Administration (2.5), Drug Interactions (7)].

5.8 Precipitation of Hepatic Encephalopathy

Drugs affecting GABA receptors, such as zolpidem tartrate, have been associated with precipitation of hepatic encephalopathy in patients with hepatic insufficiency. In addition, patients with hepatic insufficiency do not clear zolpidem tartrate as rapidly as patients with normal hepatic function. Avoid Zolpidem Tartrate Capsules use in patients with severe hepatic impairment as it may contribute to encephalopathy [see Dosage and Administration (2.1), Use in Specific Populations (8.7), Clinical Pharmacology (12.3)].

5.9 Withdrawal Effects

There have been reports of withdrawal signs and symptoms following the rapid dose decrease or abrupt discontinuation of zolpidem tartrate. Monitor patients for tolerance, abuse, and dependence [see Drug Abuse and Dependence (9.2, 9.3)].

6 ADVERSE REACTIONS

The following serious adverse reactions are discussed in greater detail in other sections of the labeling:

- Complex Sleep Behaviors [see Warnings and Precautions (5.1)]
- CNS-Depressant Effects and Next-Day Impairment [see Warnings and Precautions (5.2)]
- Severe Anaphylactic and Anaphylactoid Reactions [see Warnings and Precautions (5.4)]
- Abnormal Thinking and Behavior Changes [see Warnings and Precautions (5.5)]
- Withdrawal Effects [see Warnings and Precautions (5.9)]

6.1 Clinical Trials Experience

Because clinical studies are conducted under widely varying conditions, adverse reaction rates observed in the clinical studies of a drug cannot be directly compared to rates in the clinical studies of another drug and may not reflect the rates observed in practice.

The safety of Zolpidem Tartrate Capsules 7.5 mg for the short-term treatment of transient insomnia characterized by difficulties with sleep initiation in adults is based upon adequate and well-controlled studies of zolpidem tartrate tablets immediate-release [see Clinical Studies (14)]. The results of these adequate and well-controlled studies are presented below.

Adverse Reactions Leading to Discontinuation of Treatment

Approximately 4% of 1,701 patients who received zolpidem tartrate tablets immediate-release at all doses in U.S. premarketing clinical trials discontinued treatment because of an adverse reaction. Reactions most commonly associated with discontinuation from U.S. trials were daytime drowsiness (0.5%), dizziness (0.4%), headache (0.5%), nausea (0.6%), and vomiting (0.5%).

Approximately 4% of 1,959 patients who received zolpidem tartrate tablets immediate-release at all doses in similar foreign trials discontinued treatment because of an adverse reaction. Reactions most commonly associated with discontinuation from these trials were daytime drowsiness (1.1%), dizziness/vertigo (0.8%), amnesia (0.5%), nausea (0.5%), headache (0.4%), and falls (0.4%).

Data from a clinical study in which selective serotonin reuptake inhibitor (SSRI)-treated patients were given zolpidem tartrate revealed that four of the seven discontinuations during double-blind treatment with zolpidem tartrate (n=95) were associated with impaired concentration, continuing or aggravated depression, and manic reaction; one patient treated with placebo (n=97) was discontinued after an attempted suicide.

Most Commonly Observed Adverse Reactions in Controlled Trials

During short-term treatment (up to 10 nights) with zolpidem tartrate tablets immediate-release at doses up to 10 mg, the most commonly observed adverse reactions associated with the use of zolpidem tartrate tablets immediate-release and seen at statistically significant differences from placebo-treated patients were drowsiness (reported by 2% of zolpidem tartrate-treated patients), dizziness (1%), and diarrhea (1%).

Adverse Reactions Observed at an Incidence of ≥1% in Controlled Trials

The following tables enumerate adverse reactions frequencies that were observed at an incidence equal to 1% or greater among zolpidem tartrate-treated patients with insomnia and at a greater incidence than placebo-treated patients in U.S. placebo-controlled trials.

Table 1 was derived from results of 11 placebo-controlled short-term U.S. efficacy trials involving zolpidem tartrate tablets immediate-release.

Table 1: Adverse Reactions (≥1% and > placebo) in Placebo-Controlled Clinical Trials Zolpidem Tartrate Tablets Immediate-Release Lasting up to 10 Nights (percentage of patients reporting)
Body System Adverse Reaction | Zolpidem Tartrate Tablets Immediate-Release (≤10 mg)* (N=685) % | Placebo (N=473) %
Central and Peripheral Nervous System
Headache | 7 | 6
Drowsiness | 2 | -
Dizziness | 1 | -
Gastrointestinal System
Diarrhea | 1 | -
* Zolpidem Tartrate Capsules are available only as a 7.5 mg dosage strength.

Dose-Related Adverse Reactions

There is evidence from dose comparison trials suggesting a dose relationship for many of the adverse reactions associated with zolpidem tartrate tablets immediate-release use, particularly for certain CNS and gastrointestinal adverse reactions.

Adverse Reactions During the Premarketing Evaluation of Zolpidem Tartrate Immediate-Release

Zolpidem tartrate immediate-release was administered to 3,660 patients in clinical trials throughout the U.S., Canada, and Europe.

The frequencies presented, therefore, represent the proportions of the 3,660 patients exposed to zolpidem tartrate, at all doses, who experienced an event of the type cited on at least one occasion while receiving zolpidem tartrate immediate-release. All reported adverse reactions are included, except those already listed in the table above of adverse reactions in placebo-controlled studies, those coding terms that are so general as to be uninformative, and those events where a drug cause was remote. It is important to emphasize that, although the events reported did occur during treatment with zolpidem tartrate, they were not necessarily caused by it.

Adverse reactions are further classified within body system categories and enumerated in order of decreasing frequency using the following definitions: frequent adverse reactions are defined as those that occurred in greater than 1/100 patients; infrequent adverse reactions are those that occurred in 1/100 to 1/1,000 patients; rare reactions are those that occurred in less than 1/1,000 patients.

Autonomic nervous system: dry mouth; Infrequent: increased sweating, pallor, postural hypotension, syncope. Rare: abnormal accommodation, altered saliva, flushing, glaucoma, hypotension, impotence, increased saliva, tenesmus.

Body as a whole: back pain, chest pain, influenza-like symptoms; Frequent: asthenia. Infrequent: edema, falling, fatigue, fever, malaise, trauma. Rare: allergic reaction, allergy aggravated, anaphylactic shock, face edema, hot flashes, increased ESR, pain, restless legs, rigors, tolerance increased, weight decrease.

Cardiovascular system: palpitation; Infrequent: cerebrovascular disorder, hypertension, tachycardia. Rare: angina pectoris, arrhythmia, arteritis, circulatory failure, extrasystoles, hypertension aggravated, myocardial infarction, phlebitis, pulmonary embolism, pulmonary edema, varicose veins, ventricular tachycardia.

Central and peripheral nervous system: abnormal dreams, amnesia, depression, drugged feeling, lethargy, lightheadedness, sleep disorder; Frequent: ataxia, confusion, euphoria, insomnia, vertigo. Infrequent: agitation, anxiety, decreased cognition, detached, difficulty concentrating, dysarthria, emotional lability, hallucination, hypoesthesia, illusion, leg cramps, migraine, nervousness, paresthesia, sleeping (after daytime dosing), speech disorder, stupor, tremor. Rare: abnormal gait, abnormal thinking, aggressive reaction, apathy, appetite increased, decreased libido, delusion, dementia, depersonalization, dysphasia, feeling strange, hypokinesia, hypotonia, hysteria, intoxicated feeling, manic reaction, neuralgia, neuritis, neuropathy, neurosis, panic attacks, paresis, personality disorder, somnambulism, suicide attempts, tetany, yawning.

Gastrointestinal system: abdominal pain; Frequent: dyspepsia, hiccup, nausea. Infrequent: anorexia, constipation, dysphagia, flatulence, gastroenteritis, vomiting. Rare: enteritis, eructation, esophagospasm, gastritis, hemorrhoids, intestinal obstruction, rectal hemorrhage, tooth caries.

Hematologic and lymphatic system: Rare: anemia, hyperhemoglobinemia, leukopenia, lymphadenopathy, macrocytic anemia, purpura, thrombosis.

Immunologic system: Infrequent: infection. Rare: abscess herpes simplex herpes zoster, otitis externa, otitis media.

Liver and biliary system: Infrequent: abnormal hepatic function, increased SGPT. Rare: bilirubinemia, increased SGOT.

Metabolic and nutritional: Infrequent: hyperglycemia, thirst. Rare: gout, hypercholesteremia, hyperlipidemia, increased alkaline phosphatase, increased BUN, periorbital edema.

Musculoskeletal system: Frequent: arthralgia, myalgia. Infrequent: arthritis. Rare: arthrosis, muscle weakness, sciatica, tendinitis.

Reproductive system: Infrequent: menstrual disorder, vaginitis. Rare: breast fibroadenosis, breast neoplasm, breast pain.

Respiratory system: pharyngitis, sinusitis; Frequent: upper respiratory infection, lower respiratory infection. Infrequent: bronchitis, coughing, dyspnea, rhinitis. Rare: bronchospasm, respiratory depression, epistaxis, hypoxia, laryngitis, pneumonia.

Skin and appendages: rash; Infrequent: pruritus. Rare: acne, bullous eruption, dermatitis, furunculosis, injection-site inflammation, photosensitivity reaction, urticaria.

Special senses: Frequent: diplopia, vision abnormal. Infrequent: eye irritation, eye pain, scleritis, taste perversion, tinnitus. Rare: conjunctivitis, corneal ulceration, lacrimation abnormal, parosmia, photopsia.

Urogenital system: Frequent: urinary tract infection. Infrequent: cystitis, urinary incontinence. Rare: acute renal failure, dysuria, micturition frequency, nocturia, polyuria, pyelonephritis, renal pain, urinary retention.

6.2 Postmarketing Experience

The following adverse reactions have been identified during postapproval use of zolpidem tartrate. Because these reactions are reported voluntarily from a population of uncertain size, it is not always possible to reliably estimate their frequency or establish a causal relationship to drug exposure.

Liver and biliary system: acute hepatocellular, cholestatic or mixed liver injury with or without jaundice (i.e., bilirubin >2 × ULN, alkaline phosphatase ≥2 × ULN, transaminase ≥5 × ULN).

Psychiatric disorders: delirium

7 DRUG INTERACTIONS

Table 2 presents clinically important drug interactions with zolpidem tartrate.

Table 2: Clinically Important Drug Interactions with Zolpidem Tartrate Capsules
Alcohol and Other CNS Depressants
Clinical Impact | Concomitant use of alcohol or other CNS depressants with zolpidem tartrate may lead to additive impairment of psychomotor performance and risk of CNS depression [see Clinical Pharmacology (12.3)].
Intervention | Dosage adjustments of Zolpidem Tartrate Capsules and of other concomitant CNS depressants may be necessary when Zolpidem Tartrate Capsules are coadministered because of the potentially additive effects. Use another zolpidem tartrate immediate-release product for the 5 mg dose of zolpidem tartrate immediate-release. Refer to the Prescribing Information of other zolpidem tartrate immediate-release products for the recommended dosage for those products. The use of Zolpidem Tartrate Capsules with other sedative-hypnotics (including other zolpidem products) at bedtime or the middle of the night is not recommended [see Dosage and Administration (2.5), Warnings and Precautions (5.1, 5.2)].
Opioids
Clinical Impact | Concomitant administration of zolpidem tartrate and opioids may increase the risk of respiratory depression [see Warnings and Precautions (5.2, 5.7)].
Intervention | Limit dosage and duration of concomitant use of Zolpidem Tartrate Capsules and opioids, and monitor patients closely for respiratory depression. Consider using another zolpidem tartrate immediate-release product for a lower zolpidem tartrate dose (5 mg) [see Dosage and Administration (2.5)].
Imipramine and Chlorpromazine
Clinical Impact | Concomitant use of imipramine or chlorpromazine with zolpidem tartrate may lead to an additive effect of decreased alertness and psychomotor performance [see Clinical Pharmacology (12.3)].
Intervention | Consider using another zolpidem tartrate immediate-release product for a lower zolpidem tartrate dose (5 mg).
Sertraline
Clinical Impact | Concomitant administration of zolpidem and sertraline increases exposure to zolpidem [see Clinical Pharmacology (12.3)].
Intervention | Consider using another zolpidem tartrate immediate-release product for a lower zolpidem tartrate dose (5 mg).
CYP3A4 Inducers
Clinical Impact | Concomitant use with CYP3A4 inducers may decrease zolpidem exposure [see Clinical Pharmacology (12.3)].
Intervention | Concomitant use of Zolpidem Tartrate Capsules and CYP3A4 inducers is not recommended.
CYP3A4 Inhibitors
Clinical Impact | Concomitant use with CYP3A4 inhibitors increased zolpidem exposure [see Clinical Pharmacology (12.3)].
Intervention | Consider using another zolpidem tartrate immediate-release product for a lower zolpidem tartrate dose.

8 USE IN SPECIFIC POPULATIONS

8.1 Pregnancy

Pregnancy Exposure Registry

There is a pregnancy exposure registry that monitors pregnancy outcomes in women exposed to psychiatric medications during pregnancy. Healthcare providers are encouraged to register patients by calling the National Pregnancy Registry for Psychiatric Medications at 1-866-961-2388 or by visiting online at https://womensmentalhealth.org/research/pregnancyregistry.

Risk Summary

Neonates born to mothers using zolpidem tartrate late in the third trimester of pregnancy have been reported to experience symptoms of respiratory depression and sedation [see Clinical Considerations and Data]. Published data on the use of zolpidem tartrate during pregnancy have not reported a clear association with zolpidem and major birth defects [see Data]. Oral administration of zolpidem to pregnant rats and rabbits did not indicate a risk for adverse effects on fetal development at clinically relevant doses [see Data].

The estimated background risk of major birth defects and miscarriage for the indicated populations are unknown. All pregnancies have a background risk of birth defect, loss, or other adverse outcomes. In the U.S. general population, the estimated background risk of major birth defects and miscarriage in clinically recognized pregnancies is 2% to 4% and 15% to 20%, respectively.

Clinical Considerations

Fetal/Neonatal Adverse Reactions

Zolpidem crosses the placenta and may produce respiratory depression and sedation in neonates. Monitor neonates exposed to Zolpidem Tartrate Capsules during pregnancy and labor for signs of excess sedation, hypotonia, and respiratory depression and manage accordingly.

Data

Human Data

Published data from observational studies, birth registries, and case reports on the use of zolpidem tartrate during pregnancy do not report a clear association with zolpidem tartrate and major birth defects.

There are limited postmarketing reports of severe to moderate cases of respiratory depression that occurred after birth in neonates whose mothers had taken zolpidem tartrate during pregnancy. These cases required artificial ventilation or intratracheal intubation. The majority of neonates recovered within hours to a few weeks after birth once treated.

Zolpidem tartrate has been shown to cross the placenta.

Animal Data

Oral administration of zolpidem tartrate to pregnant rats during the period of organogenesis at 4, 20, and 100 mg base/kg/day, which are approximately 5, 25, and 120 times the maximum recommended zolpidem tartrate human dose (MRHD) of 10 mg/day (8 mg zolpidem base) based on mg/m^2 body surface area, caused delayed fetal development (incomplete fetal skeletal ossification) at maternally toxic (ataxia) doses 25 and 120 times the MRHD based on mg/m^2 body surface area.

Oral administration of zolpidem to pregnant rabbits during the period of organogenesis at 1, 4, and 16 mg base/kg/day, which are approximately 2.5, 10, and 40 times the MRHD of 10 mg/day (8 mg zolpidem base) based on mg/m^2 body surface area caused embryo-fetal death and delayed fetal development (incomplete fetal skeletal ossification) at a maternally toxic (decreased body weight gain) dose 40 times the MRHD based on mg/m^2 body surface area.

Oral administration of zolpidem tartrate to pregnant rats from day 15 of gestation through lactation at 4, 20, and 100 mg base/kg/day, which are approximately 5, 25, and 120 times the MRHD of 10 mg/day (8 mg zolpidem base) based on mg/m^2 body surface area, delayed offspring growth and decreased survival at doses 25 and 120 times, respectively, the MRHD based on mg/m^2 body surface area.

8.2 Lactation

Risk Summary

Limited data from published literature report the presence of zolpidem tartrate in human milk. There are reports of excess sedation in infants exposed to zolpidem tartrate through breastmilk [see Clinical Considerations]. There is no information on the effects of zolpidem tartrate on milk production. The developmental and health benefits of breastfeeding should be considered along with the mother's clinical need for Zolpidem Tartrate Capsules and any potential adverse effects on the breastfed infant from Zolpidem Tartrate Capsules or from the underlying maternal condition.

Clinical Considerations

Infants exposed to zolpidem tartrate through breastmilk should be monitored for excess sedation, hypotonia, and respiratory depression. A lactating woman may consider interrupting breastfeeding and pumping and discarding breast milk during treatment and for 23 hours (approximately 5 elimination half-lives) after Zolpidem Tartrate Capsules administration in order to minimize drug exposure to a breast fed infant.

8.4 Pediatric Use

Zolpidem Tartrate Capsules are not recommended for use in pediatric patients. The safety and effectiveness of Zolpidem Tartrate Capsules in pediatric patients have not been established.

In an 8-week study in pediatric patients (aged 6 to 17 years) with insomnia associated with attention-deficit/hyperactivity disorder (ADHD) an oral solution of zolpidem tartrate dosed at 0.25 mg/kg at bedtime did not decrease sleep latency compared to placebo. Psychiatric and nervous system disorders comprised the most frequent (>5%) adverse reactions observed with zolpidem tartrate versus placebo and included dizziness (24% vs 2%), headache (13% vs 9%), and hallucinations 7% vs. 0%) [see Warnings and Precautions (5.5)]. Ten (7%) pediatric patients treated with zolpidem tartrate discontinued treatment due to an adverse reaction.

8.5 Geriatric Use

Zolpidem Tartrate Capsules are not indicated in geriatric patients. Avoid use of Zolpidem Tartrate Capsules 7.5 mg in geriatric patients because necessary dosage adjustment is not possible with the available dosage strength.

Adverse reactions related to impaired motor and/or cognitive performance and unusual sensitivity to sedative/hypnotic drugs, including zolpidem, have been reported in geriatric patients [see Warnings and Precautions (5.2)].

A total of 154 patients in controlled clinical trials in the U.S. and 897 patients in clinical trials outside the U.S. who received zolpidem tartrate were ≥60 years of age. In the pool of U.S. patients ≥60 years of age who received zolpidem tartrate at dosage of ≤10 mg or placebo (taken once nightly), the following adverse reactions occurred at an incidence of at least 3% in the zolpidem tartrate-treated patients and for which the incidence in zolpidem tartrate-treated patients was at least twice the incidence in placebo-treated patients, i.e., they could be considered drug related (see Table 3).

Table 3: Adverse Reactions (≥3% and at least twice placebo) in Pooled Placebo-Controlled Clinical Trials Zolpidem Tartrate Immediate-Release in Adults ≥60 Years of Age
Adverse Reaction | Zolpidem (≤10 mg)* | Placebo
Dizziness | 3% | 0%
Drowsiness | 5% | 2%
Diarrhea | 3% | 1%
* Zolpidem Tartrate Capsules are only available as a 7.5 mg dosage strength.

A total of 30/1,959 (1.5%) zolpidem tartrate-treated non-U.S. patients reported falls, including 28/30 (93%) who were ≥70 years of age. Of these 28 patients, 23 (82%) received zolpidem tartrate dosages greater than the maximum recommended dosage (i.e., >10 mg once nightly). A total of 24/1,959 (1.2%) zolpidem tartrate-treated non-U.S. patients reported confusion, including 18/24 (75%) who were ≥70 years of age. Of these 18 patients, 14 (78%) received zolpidem tartrate dosage greater than the maximum recommended dosage (i.e., >10 mg once nightly). Zolpidem Tartrate Capsules are not indicated for use in geriatric patients. Avoid use of Zolpidem Tartrate Capsules in geriatric patients.

In several studies, Tmax, T1/2, and AUC of zolpidem tartrate were significantly higher in geriatric subjects when compared to younger adult subjects. In one study of 8 subjects (>70 years of age), the means for Cmax, T1/2, and AUC significantly increased by 50% (255 vs 384 ng/mL), 32% (2.2 vs 2.9 hr), and 64% (955 vs 1,562 ng∙hr/mL), respectively, as compared to adults (20 to 40 years of age) following a single 20 mg oral dose (two times the maximum recommended dose). Zolpidem Tartrate Capsules are not indicated for use in geriatric patients.

8.6 Males and Females

Use another zolpidem tartrate immediate-release product when initiating zolpidem tartrate immediate-release treatment in females. A lower recommended starting dosage is recommended in females (compared to males) because zolpidem blood levels are higher in females compared to males [see Dosage and Administration (2.1, 2.2)].

Females clear zolpidem tartrate from the body at a lower rate than males. Cmax and AUC parameters of zolpidem were approximately 45% higher after administration of the same zolpidem tartrate dose in females compared with males [see Clinical Pharmacology (12.3)].

8.7 Hepatic Impairment

Avoid use of Zolpidem Tartrate Capsules in patients with mild to moderate hepatic impairment (Child-Pugh score between 5 and 9), because necessary dosage adjustment is not possible with available dosage strength. Avoid use of Zolpidem Tartrate Capsules in patients with severe hepatic impairment (Child-Pugh score ≥ 10) as it may contribute to encephalopathy [see Warnings and Precautions (5.8), Clinical Pharmacology (12.3)].

9 DRUG ABUSE AND DEPENDENCE

9.1 Controlled Substance

Zolpidem Tartrate Capsules contain zolpidem tartrate, a Schedule IV controlled substance.

9.2 Abuse

Abuse and addiction are separate and distinct from physical dependence and tolerance.

Abuse is the intentional, non-therapeutic use of a drug, even once, for its desirable psychologoical or physiological effects.

Misuse is the intentional use, for therapeutic purposes, of a drug by an individual in a way other than prescribed by a health care provider or for whom is was not prescribed.

Drug addiction is a cluster of behavioral, cognitive, and physiological phenomena that may include a strong desire to take the drug, difficulties in controlling drug use (e.g., continuing drug use despite harmful consequences, giving a higher priority to drug use than other activities and obligations), and possible tolerance or physical dependence.

Studies of abuse potential in former drug abusers found that the effects of single doses of zolpidem tartrate 40 mg (4 times the maximum recommended dosage for zolpidem tartrate immediate-release) were similar, but not identical, to diazepam 20 mg, while zolpidem tartrate 10 mg was difficult to distinguish from placebo.

Because persons with a history of addiction to, or abuse of, drugs or alcohol are at increased risk for misuse, abuse and addiction of zolpidem tartrate, they should be monitored carefully when receiving Zolpidem Tartrate Capsules.

9.3 Dependence

Use of Zolpidem Tartrate Capsules may lead to the development of physical and/or psychological dependence. The risk of dependence increases with dose and duration of treatment. The risk of abuse and dependence is also greater in patients with a history of alcohol or drug abuse. Zolpidem Tartrate Capsules should be used with extreme caution in patients with current or past alcohol or drug abuse.

Physical dependence is a state that develops as a result of physiological adaptation in response to repeated drug use, manifested by withdrawal signs and symptoms after abrupt discontinuation or a significant dose reduction of a drug.

Tolerance is a physiological state characterized by a reduced response to a drug after repeated administration (i.e., a higher dose of a drug is required to produce the same effect that was once obtained at a lower dose).

Sedative/hypnotics have produced withdrawal signs and symptoms following abrupt discontinuation. These reported symptoms range from mild dysphoria and insomnia to a withdrawal syndrome that may include abdominal and muscle cramps, vomiting, sweating, tremors, convulsions, and delirium.

The following adverse reactions, which are considered to meet the DSM-III-R criteria for uncomplicated sedative/hypnotic withdrawal, were reported during clinical trials with another zolpidem tartrate immediate-release product following placebo substitution occurring within 48 hours following last zolpidem treatment: fatigue, nausea, flushing, lightheadedness, uncontrolled crying, emesis, stomach cramps, panic attack, nervousness, and abdominal discomfort. These reported adverse reactions occurred at an incidence of 1% or less. However, available data cannot provide a reliable estimate of the incidence, if any, of dependence during treatment at recommended doses. There have been postmarketing reports of abuse, dependence and withdrawal with zolpidem.

10 OVERDOSAGE

Signs and Symptoms

In postmarketing experience of overdose with zolpidem tartrate alone, or in combination with CNS-depressant agents, impairment of consciousness ranging from somnolence to coma, cardiovascular and/or respiratory compromise, and fatal outcomes have been reported.

Recommended Treatment

General symptomatic and supportive measures should be used along with immediate gastric lavage where appropriate. Intravenous fluids should be administered as needed. Zolpidem tartrate's sedative hypnotic effect was shown to be reduced by flumazenil and therefore may be useful; however, flumazenil administration may contribute to the appearance of neurological symptoms (convulsions). As in all cases of drug overdose, respiration, pulse, blood pressure, and other appropriate signs should be monitored and general supportive measures employed. Hypotension and CNS depression should be monitored and treated by appropriate medical intervention. Sedating drugs should be withheld following zolpidem tartrate overdosage, even if excitation occurs. The value of dialysis in the treatment of overdosage has not been determined, although hemodialysis studies in patients with renal failure receiving therapeutic doses have demonstrated that zolpidem tartrate is not dialyzable.

As with the management of all overdosage, the possibility of multiple drug ingestion should be considered. Consider contacting the Poison Help line (1-800-222-1222) or a medical toxicologist for additional overdose management recommendations.

11 DESCRIPTION

Zolpidem Tartrate Capsules 7.5 mg contains zolpidem tartrate, a gamma-aminobutyric acid (GABA) A receptor positive modulator of the imidazopyridine class.

Chemically, zolpidem is N,N,6-trimethyl-2-p-tolylimidazo[1,2-a] pyridine-3-acetamide L-(+)-tartrate. It has the following structure:

Zolpidem tartrate is a white to off-white crystalline powder, hygroscopic that is slightly soluble in water, sparingly soluble in methanol alcohol, and practically insoluble in methylene chloride. It has a molecular formula of (C19H21N3O)2 · C4H6O6 and molecular weight of 764.87 g/mol.

Zolpidem Tartrate Capsules are intended for oral administration and are available only in a 7.5 mg strength. The capsules contain 7.5 mg zolpidem tartrate, USP (equivalent to 6 mg zolpidem) and include the following inactive ingredients: gelatin, lactose monohydrate, magnesium stearate, microcrystalline cellulose, sodium starch glycolate, titanium dioxide, and the colorants FD&C Blue #1, FD&C Red #40 and FD&C Yellow #6.

12 CLINICAL PHARMACOLOGY

12.1 Mechanism of Action

Zolpidem is a GABA A receptor positive modulator presumed to exert its therapeutic effects in the short-term treatment of transient insomnia through binding to the benzodiazepine site of α1 subunit containing GABA A receptors, increasing the frequency of chloride channel opening resulting in the inhibition of neuronal excitation.

12.2 Pharmacodynamics

Zolpidem binds to GABA A receptors with greater affinity for α1 subunit relative to α2 and α3 subunit containing receptors. Zolpidem has no appreciable binding affinity for α5 subunit containing GABA A receptors. This binding profile may explain the relative absence of myorelaxant effects in animal studies. Zolpidem has no appreciable binding affinity for dopaminergic D2, serotonergic 5HT2, adrenergic, histaminergic or muscarinic receptors.

12.3 Pharmacokinetics

Absorption

Pharmacokinetics of zolpidem tartrate has been demonstrated to be linear between 5 mg and 20 mg (2 times the recommended dose of zolpidem tartrate (immediate-release).

Following a single dose administration of 7.5 mg Zolpidem Tartrate Capsules and 10 mg zolpidem tartrate immediate-release tablets in healthy volunteers under fasted conditions:

- The mean dose-normalized peak plasma concentration (Cmax) of zolpidem was 230 ng/mL for Zolpidem Tartrate Capsules and 218 ng/mL for 10 mg zolpidem tartrate immediate-release tablets.
- The mean dose-normalized area under concentration curve (AUC) of zolpidem was 942 hour*ng/mL for Zolpidem Tartrate Capsules and 956 hour*ng/mL zolpidem tartrate immediate-release tablets.

Effect of Food

Mean zolpidem Cmax and AUC decreased by 39% and 8%, respectively, with a high-fat, high-calorie meal compared to fasted conditions following administration of Zolpidem Tartrate Capsules 7.5 mg to healthy volunteers. The median time to reach zolpidem Cmax (Tmax) was prolonged from 1 hour to 2.8 hours post dose in the presence of food.

Distribution

Total protein binding was found to be 92.5 ± 0.1% and remained constant, independent of concentration between 40 and 790 ng/mL.

Elimination

Metabolism

Zolpidem tartrate is converted to inactive metabolites that are eliminated primarily by renal excretion.

Excretion

Following a single 7.5 mg dose of Zolpidem Tartrate Capsules under fasting state, the mean apparent clearance (CL/F) of the zolpidem tartrate was 15.72 L/hr (range: 5.44 to 96.71), and the mean elimination half-life was 3.70 hours (range: 1.2 to 8.3 hours).

Specific Populations

Male and Female Patients

At a given dose, zolpidem blood levels were higher in females compared to males. Females clear zolpidem tartrate from the body at a lower rate than males. Cmax and AUC parameters of zolpidem tartrate were approximately 45% higher at the same dose in females compared with males [see Dosage and Administration (2.1), Use in Specific Populations (8.6)].

Patients with Hepatic Impairment

The pharmacokinetics of zolpidem tartrate in eight patients with chronic hepatic impairment was compared to results in healthy subjects. Following a single 20 mg oral zolpidem tartrate dose, mean Cmax and AUC were found to be two times (250 vs 499 ng/mL) and five times (788 vs 4,203 ng∙hr/mL) higher, respectively, in patients with chronic hepatic impairment. Tmax did not change. The mean half-life in cirrhotic patients of 9.9 hr (range: 4.1 to 25.8 hr) was greater than that observed in subjects with normal hepatic function of 2.2 hr (range: 1.6 to 2.4 hr) [see Dosage and Administration (2.1), Warnings and Precautions (5.8), Use in Specific Populations (8.7)].

Patients with Renal Impairment

The pharmacokinetics of zolpidem tartrate was studied in 11 patients with end-stage renal failure (mean ClCr = 6.5 ± 1.5 mL/min) undergoing hemodialysis three times a week, who were dosed with zolpidem tartrate 10 mg orally each day for 14 or 21 days. No statistically significant differences were observed for Cmax, Tmax, half-life, and AUC between the first and last day of drug administration when baseline concentration adjustments were made. Zolpidem was not hemodialyzable. No accumulation of unchanged drug appeared after 14 or 21 days. Zolpidem pharmacokinetics was not significantly different in patients with renal impairment compared to those with normal renal function.

Drug Interaction Studies

CNS Depressants

Coadministration of zolpidem tartrate with other CNS depressants increases the risk of CNS depression [see Warnings and Precautions (5.2)]. Zolpidem tartrate was evaluated in healthy volunteers in single-dose interaction studies for several CNS drugs. Imipramine in combination with zolpidem produced no pharmacokinetic interaction other than a 20% decrease in peak levels of imipramine, but there was an additive effect of decreased alertness. Similarly, chlorpromazine in combination with zolpidem produced no pharmacokinetic interaction, but there was an additive effect of decreased alertness and psychomotor performance.

A study involving haloperidol and zolpidem revealed no effect of haloperidol on the pharmacokinetics or pharmacodynamics of zolpidem. The lack of a drug interaction following single-dose administration does not predict the absence of an effect following chronic administration.

An additive adverse effect on psychomotor performance between alcohol and oral zolpidem was demonstrated [see Warnings and Precautions (5.2)].

Drugs that affect drug metabolism via cytochrome P450

CYP 2D6 Inhibitors

Following five consecutive nightly doses at bedtime of oral zolpidem tartrate 10 mg in the presence of sertraline 50 mg (17 consecutive daily doses, at 7:00 am, in healthy female volunteers), zolpidem Cmax was significantly higher (43%) and Tmax was significantly decreased (-53%). Pharmacokinetics of sertraline and N-desmethylsertraline were unaffected by zolpidem.

A single-dose interaction study with zolpidem tartrate 10 mg and fluoxetine 20 mg at steady-state levels in male volunteers did not demonstrate any clinically significant pharmacokinetic or pharmacodynamic interactions. When multiple doses of zolpidem and fluoxetine were given at steady state and the concentrations evaluated in healthy females, an increase in the zolpidem half-life (17%) was observed. There was no evidence of an additive effect in psychomotor performance.

CYP3A Inhibitors

Some compounds known to inhibit CYP3A may increase exposure to zolpidem.

A single-dose interaction study with zolpidem tartrate 10 mg and itraconazole 200 mg at steady-state levels in male volunteers resulted in a 34% increase in AUC0–∞ of zolpidem tartrate. There were no pharmacodynamic effects of zolpidem tartrate detected on subjective drowsiness, postural sway, or psychomotor performance.

A single-dose interaction study with zolpidem tartrate 5 mg and ketoconazole, a potent CYP3A4 inhibitor, given as 200 mg twice daily for 2 days increased Cmax of zolpidem tartrate (30%) and the total AUC of zolpidem tartrate (70%) compared to zolpidem tartrate alone and prolonged the elimination half-life (30%) along with an increase in the pharmacodynamic effects of zolpidem tartrate [see Drug Interactions (7)].

Additionally, fluvoxamine (a strong inhibitor of CYP1A2 and a weak inhibitor of CYP3A4 and CYP2C9) and ciprofloxacin (a strong inhibitor of CYP1A2 and a moderate inhibitor of CYP3A4) are also likely to inhibit zolpidem’s metabolic pathways, potentially leading to an increase in zolpidem exposure.

CYP3A Inducers

A single-dose interaction study with zolpidem tartrate 10 mg and rifampin 600 mg at steady-state levels in female subjects showed significant reductions of the AUC (-73%), Cmax (-58%), and T1/2 (-36%) of zolpidem together with significant reductions in the pharmacodynamic effects of zolpidem tartrate. Rifampin, a CYP3A4 inducer, significantly reduced the exposure to and the pharmacodynamic effects of zolpidem [see Drug Interactions (7)].

Similarly, St. John’s wort, a CYP3A4 inducer, may also decrease the blood levels of zolpidem.

Cimetidine and Ranitidine

A study involving cimetidine/zolpidem tartrate and ranitidine/zolpidem tartrate combinations revealed no effect of either drug on the pharmacokinetics or pharmacodynamics of zolpidem.

Effect of Zolpidem Tartrate on Other Drugs

Zolpidem tartrate had no effect on digoxin pharmacokinetics and did not affect prothrombin time when given with warfarin in healthy subjects.

13 NONCLINICAL TOXICOLOGY

13.1 Carcinogenesis, Mutagenesis, Impairment of Fertility

Carcinogenesis

Zolpidem was administered to mice and rats for 2 years at oral doses of 4, 18, and 80 mg base/kg/day. In mice, these doses are approximately 2.5, 10, and 50 times the MRHD of 10 mg/day (8 mg zolpidem base) based on mg/m^2 body surface area and in rats, these doses are approximately 5, 20, and 100 times the MRHD based on mg/m^2 body surface area. No evidence of carcinogenic potential was observed in mice. In rats, renal tumors (lipoma, liposarcoma) were seen at the mid and high doses.

Mutagenesis

Zolpidem was negative in in vitro (bacterial reverse mutation, mouse lymphoma, and chromosomal aberration) and in vivo (mouse micronucleus) genetic toxicology assays.

Impairment of Fertility

Zolpidem was administered to rats at 4, 20, and 100 mg base/kg/day, which are approximately 5, 25, and 120 times the MRHD of 10 mg/day (8 mg zolpidem base) based on mg/m^2 body surface area, prior to and during mating, and continuing in females through postpartum day 25. Zolpidem caused irregular estrus cycles and prolonged precoital intervals at the highest dose tested, which is approximately 120 times the MRHD based on mg/m^2 body surface area. The NOAEL for these effects is 25 times the MRHD based on a mg/m^2 body surface area. There was no impairment of fertility at any dose tested.

14 CLINICAL STUDIES

14.1 Transient Insomnia

The efficacy of Zolpidem Tartrate Capsules for the short-term treatment of transient insomnia characterized by difficulties with sleep initiation in adult patients younger than 65 years of age is based upon adequate and well-controlled studies of zolpidem tartrate tablets (immediate-release). The results of these adequate and well-controlled studies of zolpidem tartrate tablets are presented below.

Adults experiencing transient insomnia (n=462) during the first night in a sleep laboratory were evaluated in a double-blind, parallel group, single-night trial comparing two doses of zolpidem tartrate tablets (7.5 mg and 10 mg) and placebo. Both zolpidem tartrate doses were superior to placebo on objective (polysomnographic) measures of sleep latency, sleep duration, and number of awakenings.

14.2 Studies Pertinent to Safety Concerns for Sedative/Hypnotic Drugs

Next-Day Residual Effects

Next-day residual effects of zolpidem tartrate were evaluated in seven studies involving healthy subjects. In three studies in adults (including one study in a phase advance model of transient insomnia) and in one study in elderly subjects (Zolpidem Tartrate Capsules are not indicated in geriatric patients, see Use in Specific Populations (8.5)), a small but statistically significant decrease in performance was observed in the Digit Symbol Substitution Test (DSST) when compared to placebo. Studies of zolpidem tartrate in non-elderly patients with insomnia did not detect evidence of next-day residual effects using the DSST, the Multiple Sleep Latency Test (MSLT), and patient ratings of alertness.

Rebound Effects

There was no objective (polysomnographic) evidence of rebound insomnia at recommended doses seen in studies evaluating sleep on the nights following discontinuation of zolpidem tartrate. There was subjective evidence of impaired sleep in the elderly on the first post-treatment night at doses above the 5 mg (Zolpidem Tartrate Capsules is not indicated in geriatric patients, see Use in Specific Populations (8.5)).

Memory Impairment

Controlled studies in adults utilizing objective measures of memory yielded no consistent evidence of next-day memory impairment following the administration of zolpidem tartrate. However, in one study involving zolpidem doses of 10 mg and 20 mg (2 times the maximum recommended zolpidem tartrate immediate-release dose), there was a significant decrease in next-morning recall of information presented to subjects during peak drug effect (90 minutes post dose), i.e., these subjects experienced anterograde amnesia. There was also subjective evidence from adverse event data for anterograde amnesia occurring in association with the administration of zolpidem tartrate, predominantly at doses above the maximum recommended zolipidem tartrate dose of 10 mg.

Effects on Sleep Stages

In studies that measured the percentage of sleep time spent in each sleep stage, zolpidem tartrate has generally been shown to preserve sleep stages. Sleep time spent in stages 3 and 4 (deep sleep) was found comparable to placebo with only inconsistent, minor changes in REM (paradoxical) sleep at the recommended dose.

16 HOW SUPPLIED/STORAGE AND HANDLING

Zolpidem Tartrate Capsules 7.5 mg are hard gelatin capsules with “ALM” printed axially on the opaque light green cap and “775” printed axially on the opaque white body, and available as:

NDC 52427-775-30, bottle of 30 capsules with child-resistant closure

Store at 20°C to 25°C (68°F to 77°F); excursions permitted between 15°C and 30°C (59°F to 86°F) [see USP Controlled Room Temperature].

17 PATIENT COUNSELING INFORMATION

Advise the patient to read the FDA-approved patient labeling (Medication Guide).

Complex Sleep Behaviors

Instruct patients and their families that Zolpidem Tartrate Capsules may cause complex sleep behaviors, including sleep-walking, sleep-driving, preparing and eating food, making phone calls, or having sex while not being fully awake. Serious injuries and death have occurred during complex sleep behavior episodes. Tell patients to discontinue Zolpidem Tartrate Capsules and notify their healthcare provider immediately if they develop any of these symptoms [see Boxed Warning, Warnings and Precautions (5.1)].

CNS-Depressant Effects and Next-Day Impairment

Advise patients that Zolpidem Tartrate Capsules has the potential to cause next-day impairment, and that this risk is increased if dosing instructions are not carefully followed. Tell patients to wait for at least 8 hours after dosing before driving or engaging in other activities requiring full mental alertness. Inform patients that impairment can be present despite feeling fully awake. Advise patients that increased drowsiness and decreased consciousness may increase the risk of falls in some patients [see Warnings and Precautions (5.2)].

Severe Anaphylactic and Anaphylactoid Reactions

Inform patients that severe anaphylactic and anaphylactoid reactions have occurred with zolpidem. Describe the signs/symptoms of these reactions and advise patients to seek medical attention immediately if any of them occur [see Warnings and Precautions (5.4)].

Suicide

Tell patients to immediately report any suicidal thoughts.

Alcohol and other Drugs

Ask patients about alcohol consumption, medicines they are taking, and drugs they may be taking without a prescription. Advise patients not to use Zolpidem Tartrate Capsules if they drank alcohol that evening or before bed.

Concomitant Use with Opioids

Inform patients and caregivers that potentially serious additive effects may occur if Zolpidem Tartrate Capsules are used with opioids and not to use such drugs concomitantly unless supervised by a healthcare provider [see Warnings and Precautions (5.2, 5.7), Drug Interactions (7)].

Tolerance, Abuse, and Dependence

Tell patients not to increase the dose of zolpidem tartrate on their own, and to inform you if they believe the drug “does not work.”

Administration Instructions

Patients should be counseled to take Zolpidem Tartrate Capsules right before they get into bed and only when they are able to stay in bed a full night (7 to 8 hours) before being active again. Zolpidem Tartrate Capsules should not be taken with or immediately after a meal. Advise patients NOT to take Zolpidem Tartrate Capsules if they drank alcohol that evening.

Pregnancy

Advise patients to notify their healthcare provider if they become pregnant or intend to become pregnant during treatment with Zolpidem Tartrate Capsules, and that there is a pregnancy registry that monitors pregnancy outcomes in women exposed to zolpidem tartrate. Advise patients that use of Zolpidem Tartrate Capsules late in the third trimester may cause respiratory depression and sedation in neonates. Advise mothers who used Zolpidem Tartrate Capsules during the late third trimester of pregnancy to monitor neonates for signs of sleepiness (more than usual), breathing difficulties, or limpness [see Use in Specific Populations (8.1)].

Lactation

Advise breastfeeding mothers using Zolpidem Tartrate Capsules to monitor infants for increased sleepiness, breathing difficulties, or limpness. Instruct breastfeeding mothers to seek immediate medical care if they notice these signs. A lactating female may consider pumping and discarding breastmilk during treatment and for 23 hours after Zolpidem Tartrate Capsules administration to minimize drug exposure to a breastfed infant [see Use in Specific Populations (8.2)].

Distributed by:
Almatica Pharma LLC
Morristown, NJ 07960 USA

PI775-00

MEDICATION GUIDE
ZOLPIDEM TARTRATE (zol pi dem tar trate)
CAPSULES for oral use, CIV

What is the most important information I should know about Zolpidem Tartrate Capsules?

Zolpidem Tartrate Capsules may cause serious side effects, including:

- Complex sleep behaviors. After taking Zolpidem Tartrate Capsules, you may get up out of bed while not being fully awake and do an activity that you do not know you are doing. The next morning, you may not remember that you did anything during the night. These activities may happen with Zolpidem Tartrate Capsules whether or not you drink alcohol or take other medicines that make you sleepy. Some of these complex sleep behaviors have caused serious injury and death. People taking zolpidem tartrate have reported:
  - sleep-walking
  - sleep-driving
  - making and eating food
  - talking on the phone
  - having sex

Stop taking Zolpidem Tartrate Capsules and tell your healthcare provider right away if you find out that you have done any of the above activities after taking Zolpidem Tartrate Capsules.

What are Zolpidem Tartrate Capsules?

Zolpidem Tartrate Capsules are a prescription sleep medicine used for the short-term treatment of adults younger than 65 years of age who have trouble falling asleep for a short period of time only (transient insomnia).
It is not known if Zolpidem Tartrate Capsules are safe and effective in children. Zolpidem Tartrate Capsules are not recommended for use in children or in adults over age 65.
Zolpidem Tartrate Capsules are a federally controlled substance (CIV) because they can be abused or lead to dependence. Keep Zolpidem Tartrate Capsules in a safe place to protect them from misuse and abuse and theft. Never give your Zolpidem Tartrate Capsules to anyone else because it may cause death or harm them. Selling or giving away Zolpidem Tartrate Capsules is against the law.

Do not take Zolpidem Tartrate Capsules if you:

- have had complex sleep behaviors that happened after taking zolpidem in the past. See “What is the most important information I should know about Zolpidem Tartrate Capsules?”
- are allergic to zolpidem or any of the ingredients in Zolpidem Tartrate Capsules. See the end of this Medication Guide for a complete list of ingredients in Zolpidem Tartrate Capsules.

Before taking Zolpidem Tartrate Capsules, tell your healthcare provider about all of your medical conditions, including if you:

- have a history of depression, mental illness, or suicidal thoughts or actions
- have a history of drug or alcohol abuse or addiction
- have kidney problems
- have liver problems. Zolpidem Tartrate Capsules should not be used in people with liver problems.
- have a lung disease or breathing problems
- have sleep apnea
- have myasthenia gravis
- are a female and are not currently taking another zolpidem tartrate medicine. If you have never taken a zolpidem tartrate medicine before, your healthcare provider should prescribe another product to start zolpidem tartrate.
- are pregnant or plan to become pregnant. Taking Zolpidem Tartrate Capsules in the third trimester of pregnancy may harm your unborn baby.
  - Tell your healthcare provider if you become pregnant or plan to become pregnant during treatment with Zolpidem Tartrate Capsules.
  - There is a pregnancy exposure registry for females who are exposed to psychiatric medicines during pregnancy. If you become pregnant during treatment with Zolpidem Tartrate Capsules, talk to your healthcare provider about registering you with the National Pregnancy Registry for Psychiatric Medications by calling 1-866-961-2388 or by visiting online at https://womensmentalhealth.org/research/pregnancyregistry.
  - Taking Zolpidem Tartrate Capsules during your third trimester of pregnancy may cause your baby to have breathing problems and sedation (such as unusual sleepiness or limp muscles).
- are breastfeeding or plan to breastfeed. Zolpidem tartrate passes into your breast milk and may harm your baby. Talk to your healthcare provider about the best way to feed your baby during treatment with Zolpidem Tartrate Capsules.
  - If you breastfeed during treatment with Zolpidem Tartrate Capsules:
    - call your healthcare provider or go to the nearest emergency room right away if your baby develops increased sleepiness, breathing problems, or limpness.
    - to decrease the chance of your baby getting the medicine through your breast milk, you can pump and throw away your breast milk during treatment with Zolpidem Tartrate Capsules and for 23 hours after stopping use of Zolpidem Tartrate Capsules.

Tell your healthcare provider about all of the medicines you take, including prescription and over-the-counter medicines, vitamins and herbal supplements.

Zolpidem Tartrate Capsules and other medicines can interact with each other causing serious side effects. Zolpidem Tartrate Capsules may affect the way other medicines work, and other medicines may affect how Zolpidem Tartrate Capsules works.

Especially tell your healthcare provider if you:

- take benzodiazepines
- take opioids as it may increase the risk of breathing problems (respiratory depression)
- take tricyclic antidepressants
- take other medicines that can make you sleepy or affect your breathing (including other zolpidem medicines)
- drink alcohol

If you take certain medicines, you may need to take another zolpidem tartrate medicine instead of Zolpidem Tartrate Capsules because the medicines may interact.
You can ask your pharmacist for a list of medicines that interact with Zolpidem Tartrate Capsules.

Know the medicines you take. Keep a list of them to show your healthcare provider and pharmacist when you get a new medicine.

How should I take Zolpidem Tartrate Capsules?

- Take Zolpidem Tartrate Capsules exactly as your healthcare provider tells you to take them. Do not change your dose on your own. Tell your healthcare provider if you think Zolpidem Tartrate Capsules are not working for you.
- If your sleep problems do not get better within 7 to 10 days, or if they get worse, this may mean that there is another condition causing your sleep problems.
- Zolpidem Tartrate Capsules are for short-term use only. Treatment with Zolpidem Tartrate Capsules should be as short as possible because the risk of abuse and dependence increases the longer you are being treated.
- Take 1 Zolpidem Tartrate Capsule at night right before bedtime.
- Do not take Zolpidem Tartrate Capsules if you are not able to stay in bed a full night (7 to 8 hours) before you must be active again.
- Do not take more than 1 Zolpidem Tartrate Capsule during the same night.
- Do not take Zolpidem Tartrate Capsules with food or right after a meal.
- Do not take Zolpidem Tartrate Capsules if you drank alcohol that evening or before bed.
- Swallow Zolpidem Tartrate Capsules whole. Do not open, crush, or chew the capsules.

If you take too much Zolpidem Tartrate Capsules, call your healthcare provider or Poison Help line at 1-800-222-1222 or go to the nearest hospital emergency room right away.

What are the possible side effects of Zolpidem Tartrate Capsules?

Zolpidem Tartrate Capsules may cause serious side effects, including:

- See "What is the most important information I should know about Zolpidem Tartrate Capsules?"
- Zolpidem Tartrate Capsules can make you sleepy or dizzy, can cause blurred or double vision, and can slow your thinking and motor skills. Because Zolpidem Tartrate Capsules can make you sleepy or dizzy you are at a higher risk for falls. You may still feel this way when you wake up in the morning.
  - Do not drive, operate heavy machinery, or do other dangerous activities until you know how Zolpidem Tartrate Capsules affects you.
  - Do not drink alcohol or take opioids or other medicines that may make you sleepy or dizzy while taking Zolpidem Tartrate Capsules without first talking to your healthcare provider. When taken with alcohol or other medicines that cause sleepiness or dizziness, Zolpidem Tartrate Capsules may make your sleepiness or dizziness much worse.
- Severe allergic reactions. Symptoms include swelling of the tongue or throat, trouble breathing, and nausea and vomiting. Swelling of the tongue or throat may block your ability to breathe and can lead to death. Get emergency medical help right away if you develop any of these symptoms during treatment with Zolpidem Tartrate Capsules.
- Abnormal thoughts and behavior. Symptoms include more outgoing or aggressive behavior than normal, confusion (delirium), acting or feeling strangely, agitation, and seeing or hearing things that aren’t real (hallucinations).
- Risk of suicide and worsening of depression. Worsening of depression and suicidal thoughts and actions, including completed suicides, can happen during treatment with medicines like Zolpidem Tartrate Capsules. Call your healthcare provider right away if you develop any thoughts of suicide, dying, or worsening depression during treatment with Zolpidem Tartrate Capsules.
- Breathing problems. Call your healthcare provider or get emergency medical help right away if you develop breathing problems during treatment with Zolpidem Tartrate Capsules. Certain medical conditions and medicines may increase your risk for breathing problems. See “Before taking Zolpidem Tartrate Capsules, tell your healthcare provider about all of your medical conditions, including if you:”
- Problems with your nervous system caused by severe liver disease (hepatic encephalopathy).
- Withdrawal symptoms. You may have withdrawal symptoms if you stop taking Zolpidem Tartrate Capsules suddenly. Withdrawal symptoms can be serious and include stomach and muscle cramps, vomiting, sweating, shakiness, seizures, and confusion (delirium). Talk to your healthcare provider about slowly stopping Zolpidem Tartrate Capsules to avoid withdrawal symptoms.

The most common side effects of Zolpidem Tartrate Capsules include headache, sleepiness, dizziness, and diarrhea.

These are not all the side effects of Zolpidem Tartrate Capsules.

Call your doctor for medical advice about side effects. You may report side effects to FDA at 1-800-FDA-1088.

How should I store Zolpidem Tartrate Capsules?

- Store Zolpidem Tartrate Capsules at room temperature between 68°F to 77°F (20°C to 25°C).
- Zolpidem Tartrate Capsules come in a child resistant container.

Keep Zolpidem Tartrate Capsules and all medicines out of the reach of children.

General Information about the safe and effective use of Zolpidem Tartrate Capsules.

Medicines are sometimes prescribed for purposes other than those listed in a Medication Guide. Do not use Zolpidem Tartrate Capsules for a condition for which it was not prescribed. Do not give Zolpidem Tartrate Capsules to other people, even if they have the same symptoms that you have. It may harm them. You can ask your pharmacist or healthcare provider for information about Zolpidem Tartrate Capsules that is written for health professionals.

What are the ingredients in Zolpidem Tartrate Capsules?

Active Ingredient: zolpidem tartrate

Inactive Ingredients: gelatin, lactose monohydrate, magnesium stearate, microcrystalline cellulose, sodium starch glycolate, titanium dioxide, FD&C Blue #1, FD&C Red #40 and FD&C Yellow #6

Distributed by:

Almatica Pharma LLC

Morristown, NJ 07960 USA

For more information, please call 1-877-447-7979 or visit www.almatica.com.

This Medication Guide has been approved by the U.S. Food and Drug Administration.

Issued: 5/2023
PL775-00

PRINCIPAL DISPLAY PANEL - Bottle Label

NDC 52427-775-30

Zolpidem Tartrate Capsules CIV

7.5 mg

ATTENTION PHARMACIST: Each patient is required to receive the accompanying Medication Guide.

Contains FD&C Yellow No. 6

Rx only

For oral use

30 Capsules